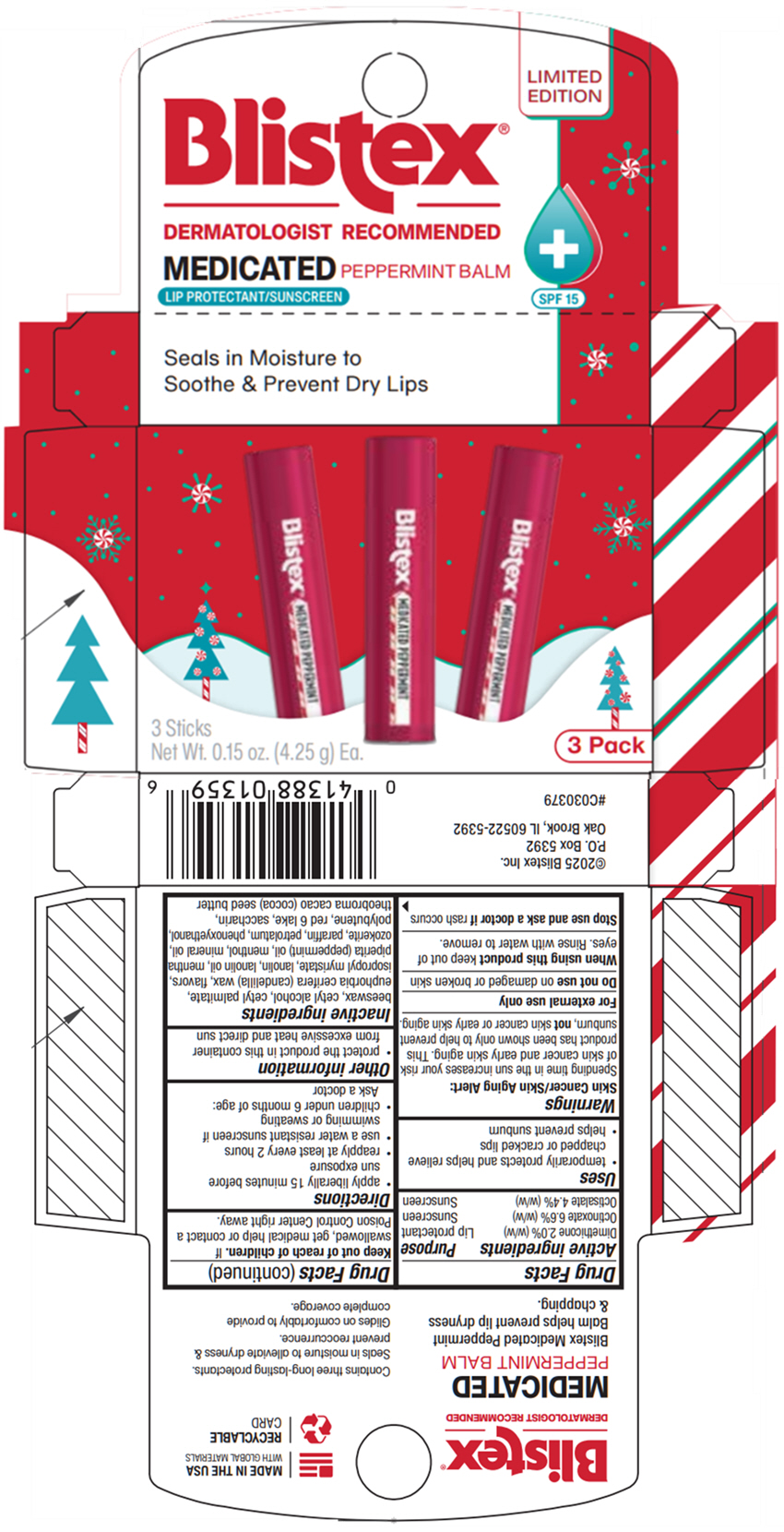 DRUG LABEL: Medicated Peppermint Lip Balm
NDC: 10157-4104 | Form: STICK
Manufacturer: Blistex Inc
Category: otc | Type: HUMAN OTC DRUG LABEL
Date: 20250718

ACTIVE INGREDIENTS: DIMETHICONE, UNSPECIFIED 2 g/100 g; OCTINOXATE 6.6 g/100 g; OCTISALATE 4.4 g/100 g
INACTIVE INGREDIENTS: PETROLATUM; MINERAL OIL; CERESIN; CANDELILLA WAX; LANOLIN OIL; YELLOW WAX; ISOPROPYL MYRISTATE; LANOLIN; POLYBUTENE (1400 MW); CETYL PALMITATE; CETYL ALCOHOL; PARAFFIN; PEPPERMINT OIL; COCOA BUTTER; PHENOXYETHANOL; SACCHARIN; MENTHOL, UNSPECIFIED FORM; D&C RED NO. 6

Medicated Peppermint Lip Balm

Drug Facts

ACTIVE INGREDIENT

Active ingredients | Purpose
Dimethicone 2.0% (w/w) | Lip protectant
Octinoxate 6.6% (w/w) | Sunscreen
Octisalate 4.4% (w/w) | Sunscreen

Uses

- temporarily protects and helps relieve chapped or cracked lips
- helps prevent sunburn

Warnings

Skin Cancer/Skin Aging Alert

Spending time in the sun increases your risk of skin cancer and early skin aging. This product has been shown only to help prevent sunburn, not skin cancer or early skin aging.

For external use only

Do not use on damaged or broken skin

When using this product keep out of eyes. Rinse with water to remove.

Stop use and ask a doctor if rash occurs

Keep out of reach of children. If swallowed, get medical help or contact a Poison Control Center right away.

Directions

- apply liberally 15 minutes before sun exposure
- reapply at least every 2 hours
- use a water resistant sunscreen if swimming or sweating
- children under 6 months of age:
  Ask a doctor

Other information

- protect the product in this container from excessive heat and direct sun

Inactive ingredients

beeswax, cetyl alcohol, cetyl palmitate, euphorbia cerifera (candelilla) wax, flavors, isopropyl myristate, lanolin, lanolin oil, mentha piperita (peppermint) oil, menthol, mineral oil, ozokerite, paraffin, petrolatum, phenoxyethanol, polybutene, red 6 lake, saccharin, theobroma cacao (cocoa) seed butter

PRINCIPAL DISPLAY PANEL - 3 Stick Carton

Blistex®

LIMITED
EDITION

DERMATOLOGIST RECOMMENDED

MEDICATED PEPPERMINT BALM
LIP PROTECTANT/SUNSCREEN

SPF 15

3 Sticks
Net Wt. 0.15 oz. (4.25 g) Ea.

3 Pack